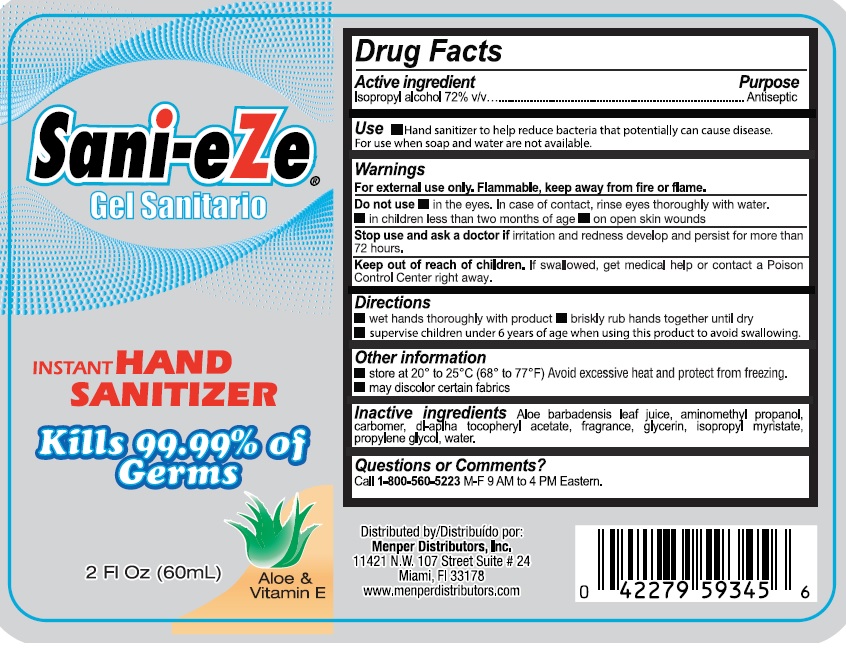 DRUG LABEL: Sani eZe
NDC: 53145-410 | Form: GEL
Manufacturer: MENPER DISTRIBUTORS, INC.
Category: otc | Type: HUMAN OTC DRUG LABEL
Date: 20210414

ACTIVE INGREDIENTS: ISOPROPYL ALCOHOL 72 mg/100 mL
INACTIVE INGREDIENTS: ALOE; AMINOMETHYLPROPANOL; CARBOMER 940; .ALPHA.-TOCOPHEROL ACETATE, DL-; GLYCERIN; ISOPROPYL MYRISTATE; PROPYLENE GLYCOL; WATER

Active Ingredient Purpose

Isopropyl alcohol 72% v/v..................Antiseptic

Purpose

Antiseptic

Use

Hand sanitizer to help reduce bacteria that potentially can cause disease.

For use when soap and water are not available.

Warnings

For external use only. Flammable keep away from fire or flame.

Do not use

in the eyes. In case of contact, rinse eyes throughly with water.
in children less than two months of age
on open skin wounds
Stop use and ask a doctor if irritation and redness develop and persist for more than 72 hours.

Keep out of reach of children. If swallowed, get medical help or contact a Posion Control Center right away.

Directions

wet hands thoroughly with product
briskly rub hands together until dry
supervise children under 6 years of age when using this product to avoid swallowing.
Other information

store at 20° to 25°C (68° to 77°F) Avoid excessive heat and protect from freezing.
may discolor certain frabics

Inactive ingredients

Aloe barbadensis leaf juice, aminomethyl propanol, carbomer, dl-alpha tocopherol acetate, fragrance, glycerin, isopropyl myristate, propylene glycol, water.

Questions or Comments?

Call 1-800-560-5223 M-F 9 AM TO 4 PM Eastern.